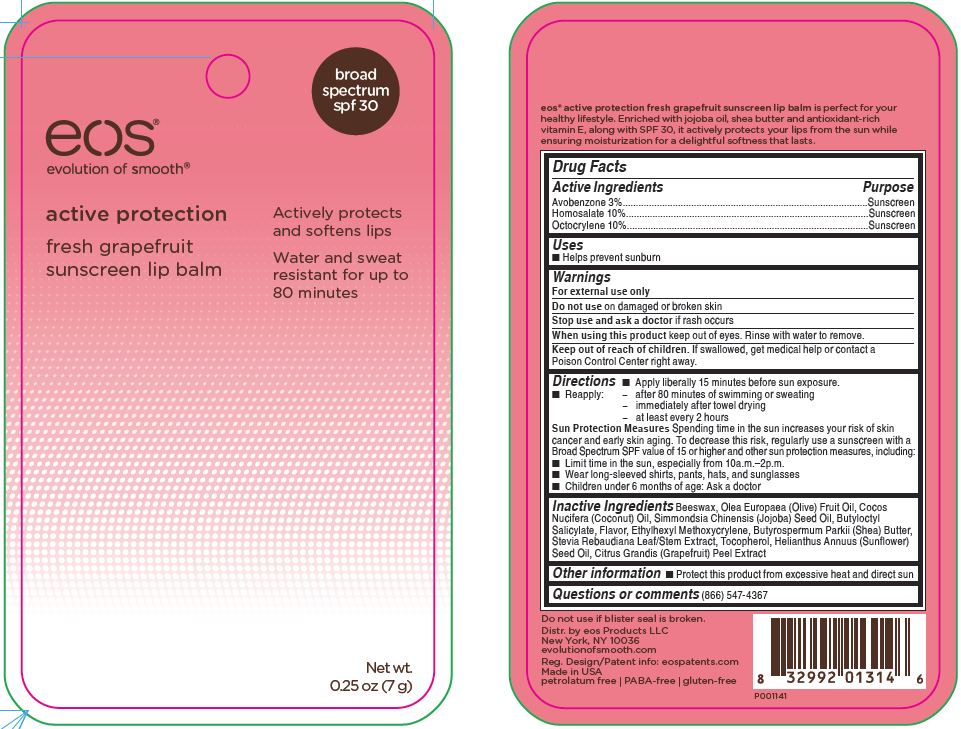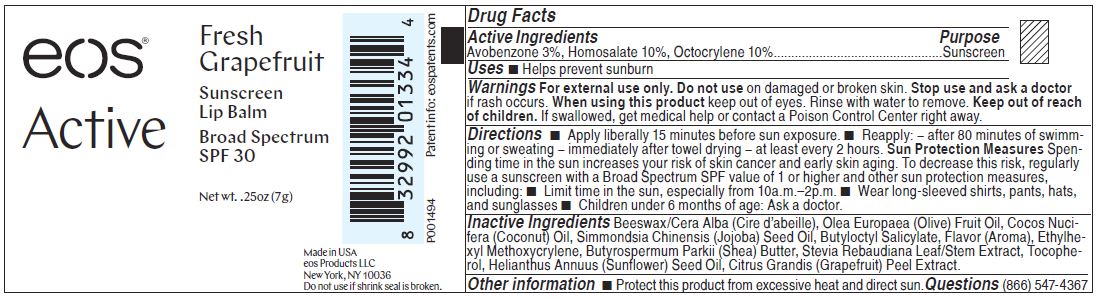 DRUG LABEL: eos active protection fresh grapefruit sunscreen lip balm broad spectrum spf 30
NDC: 70170-0009 | Form: STICK
Manufacturer: eos Products LLC
Category: otc | Type: HUMAN OTC DRUG LABEL
Date: 20170403

ACTIVE INGREDIENTS: AVOBENZONE 0.21 g/7 g; HOMOSALATE 0.7 g/7 g; OCTOCRYLENE 0.7 g/7 g
INACTIVE INGREDIENTS: YELLOW WAX; OLIVE OIL; COCONUT OIL; JOJOBA OIL; BUTYLOCTYL SALICYLATE; ETHYLHEXYL METHOXYCRYLENE; SHEA BUTTER; STEVIA REBAUDIUNA LEAF; TOCOPHEROL; SUNFLOWER OIL; CITRUS MAXIMA FRUIT RIND

eos active protection fresh grapefruit sunscreen lip balm broad spectrum spf 30

Drug Facts

Active ingredients Purpose

Avobenzone 3% Sunscreen

Homosalate 10% Sunscreen

Octocrylene 10% Sunscreen

Uses

- Helps prevent sunburn.

Warnings

For external use only.

Do not use on damages or broken skin.

When using this product keep out of eyes. Rinse with water to remove.

Stop use and ask a doctor if rash occurs.

Keep out of reach of children. If swallowed, get medical help or contact a Poison Control Center right away.

Directions

- Apply liberally 15 minutes before sun exposure
- Reapply:

- after 80 minutes of swimming or sweating

- immediately after towel drying

- at least every 2 hours

- Children under 6 months of age: Ask a doctor

Sun Protection Measures: Spending time in the sun increases your risk of skin cancer and early skin aging. To decrease this risk, regularly use a sunscreen with a Broad Spectrum SPF value of 15 or higher and other sun protection measures, including:

- Limit time in the sun, especially from 10 a.m. - 2 p.m.
- Wear long-sleeved shirts, pants, hats, and sunglasses

Inactive ingredients

Beeswax, Olea Europaea (Olive) Fruit Oil, Cocos Nucifera (Coconut) Oil, Simmondsia Chinensis (Jojoba) Seed Oil, Butyloctyl Salicylate, Flavor, Ethylhexyl Methoxycrylene, Butyrospermum Parkii (Shea) Butter, Stevia Rebaudiana Leaf/Stem Extract, Tocopherol, Helianthus Annuus (Sunflower)
Seed Oil, Citrus Grandis (Grapefruit) Peel Extract.

Other information

- Protect this product frome excessive heat and direct sun.

Questions or comments

(866) 547-4367

Principal Display Panel - 0.25 oz (7 g)

eos active protection fresh grapefruit sunscreen lip balm broad spectrum spf 30